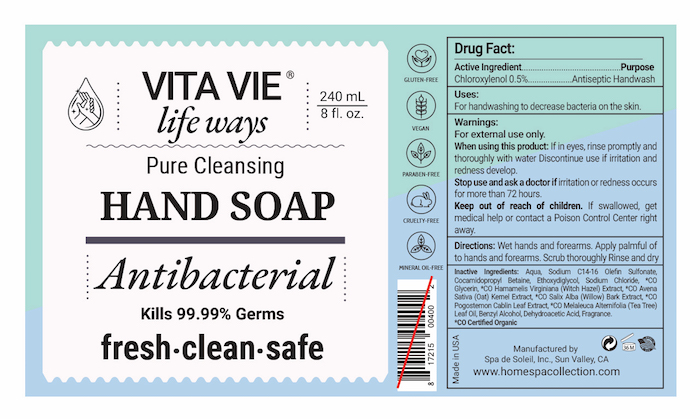 DRUG LABEL: Vitavie
NDC: 68062-2218 | Form: SOLUTION
Manufacturer: Spa De Soleil
Category: otc | Type: HUMAN OTC DRUG LABEL
Date: 20200407

ACTIVE INGREDIENTS: CHLOROXYLENOL 1.2 g/240 mL
INACTIVE INGREDIENTS: WATER; GLYCERIN

Vita Vie

Active Ingredient - Chloroxylenol 0.5%

Purpose - Antispetic Handwash

PURPOSE

Uses - For handwashing to decrease bacteria on the skin

Warnings - For external use only

When using this product avoid contact with eyes. In case of eye contact, rinse promptly and thoroughly with water.

Stop use and ask a doctor if irritation and redness occurs for more than 72 hours.

Keep out of reach of children. If swallowed, get medical help or contact a Poison Control Center right away.

INDICATIONS AND USAGE

Directions: We hands and forearms. Apply a palmful of foam to hands and lather over hands and forearms. Scrub thoroughly. Rinse and dry.

DOSAGE AND ADMINISTRATION

Repeat applications as needed.

Questions? 1-800-258-DIAL (3425)